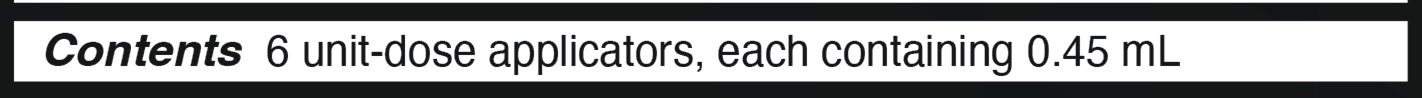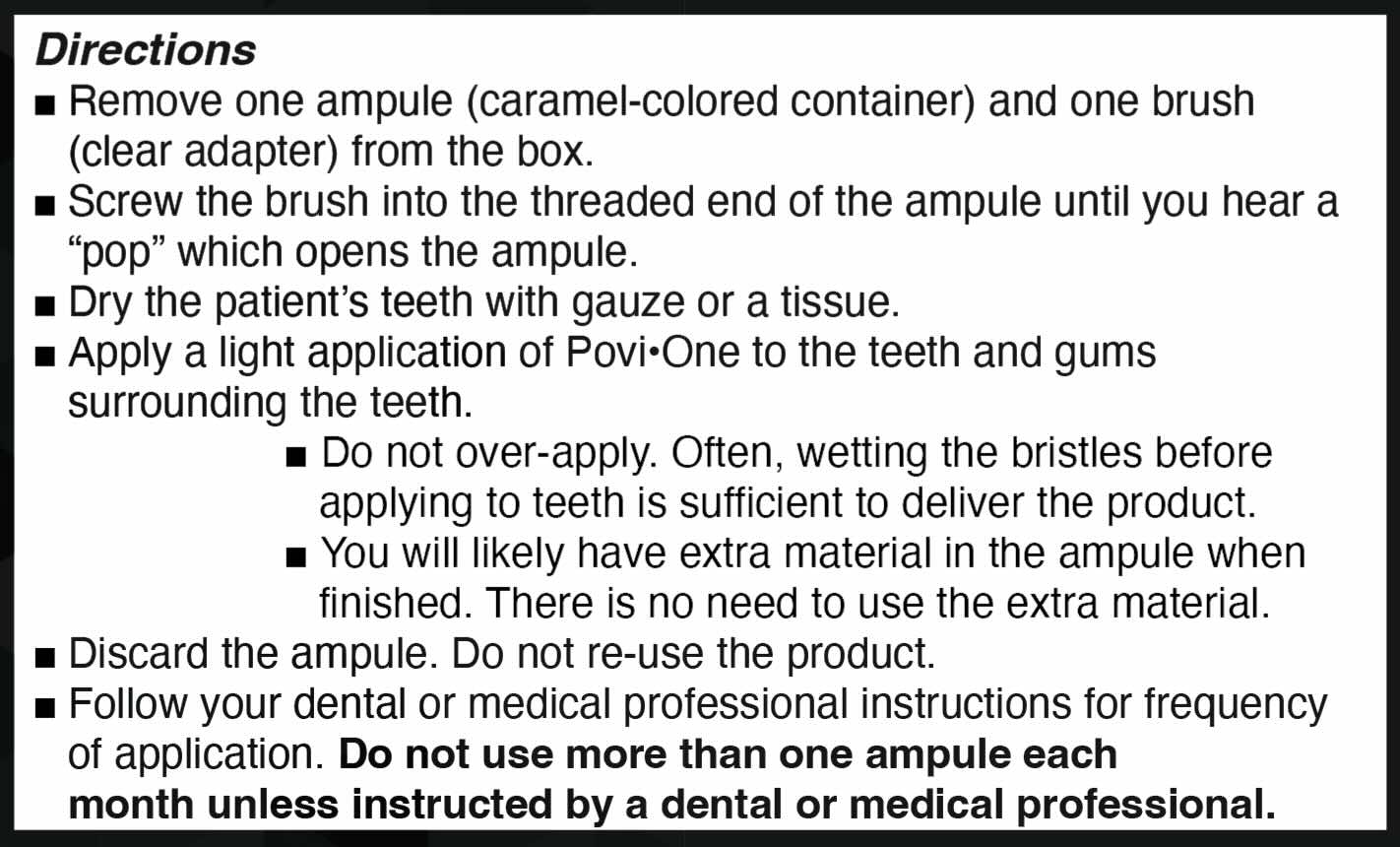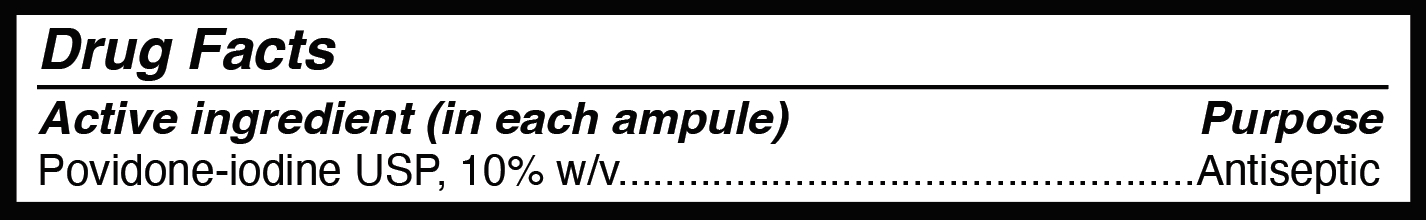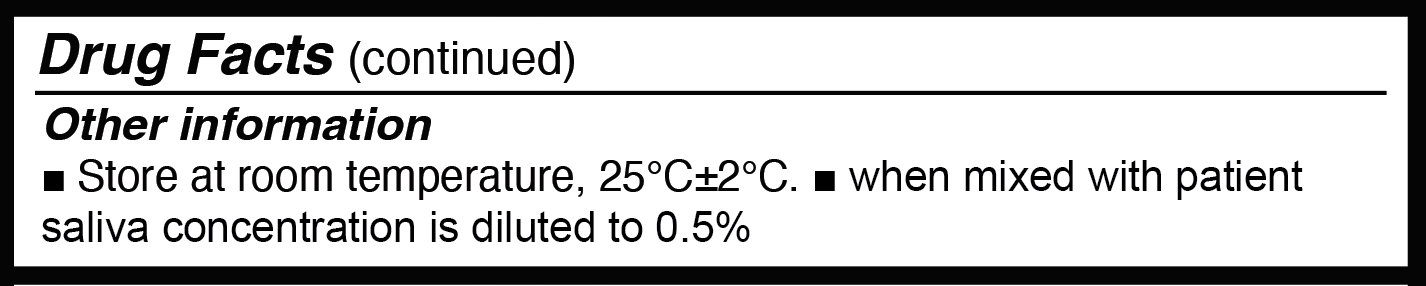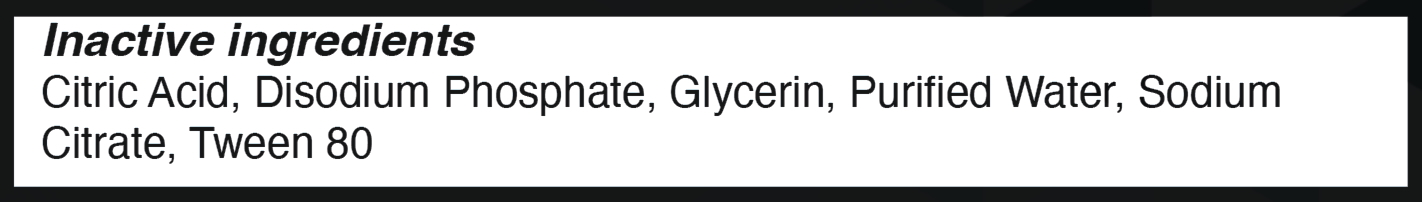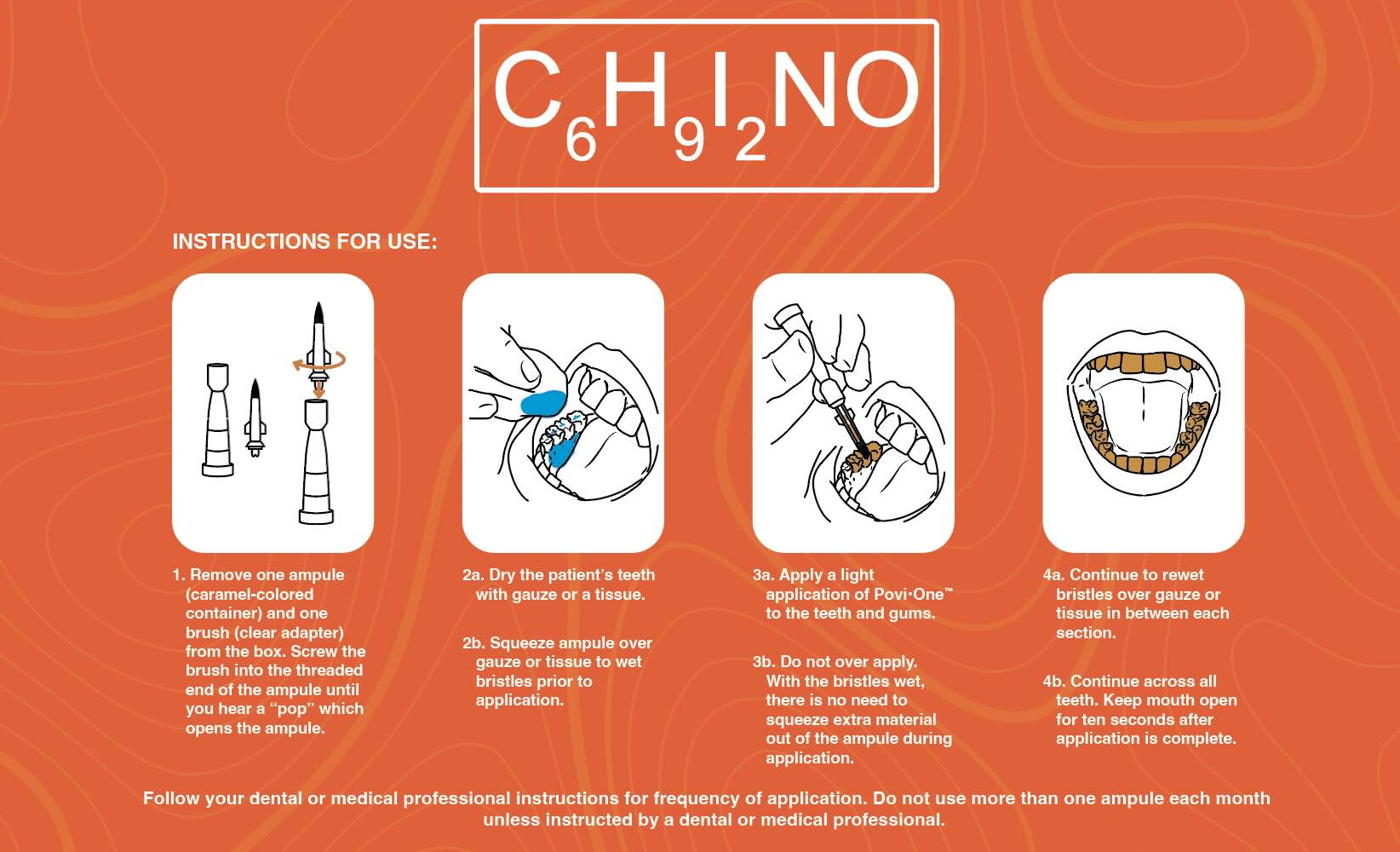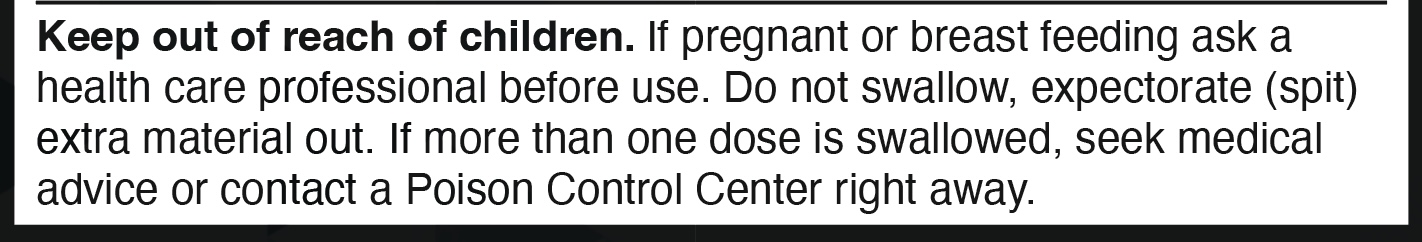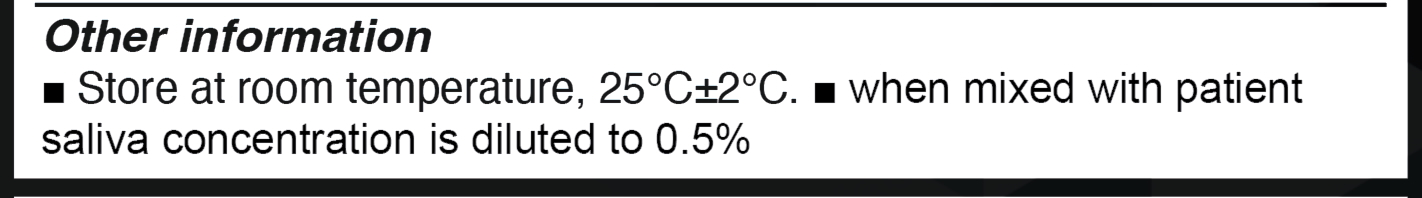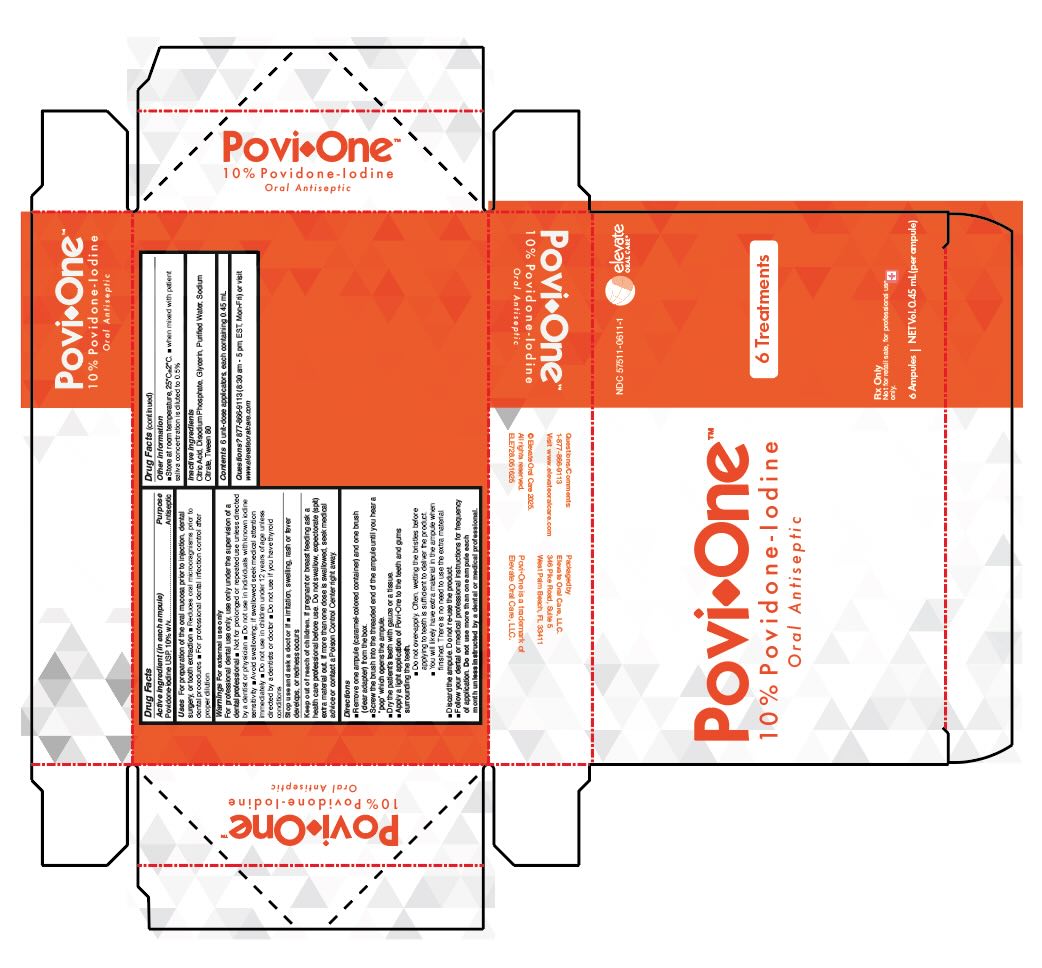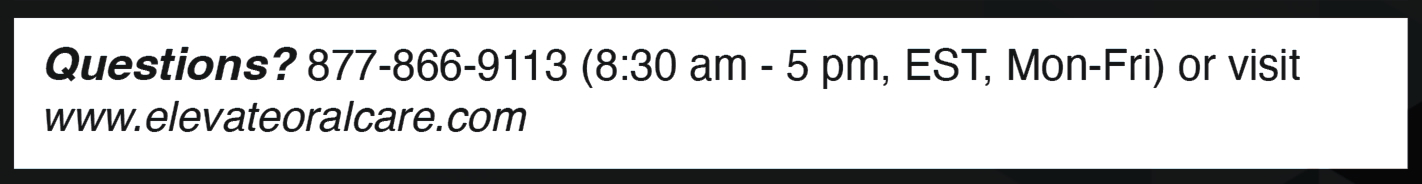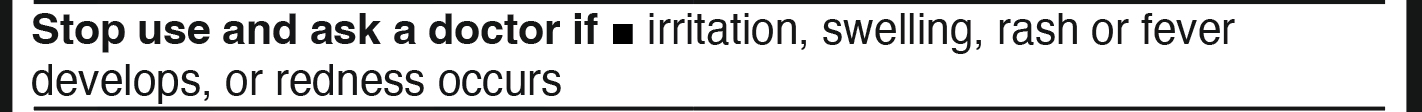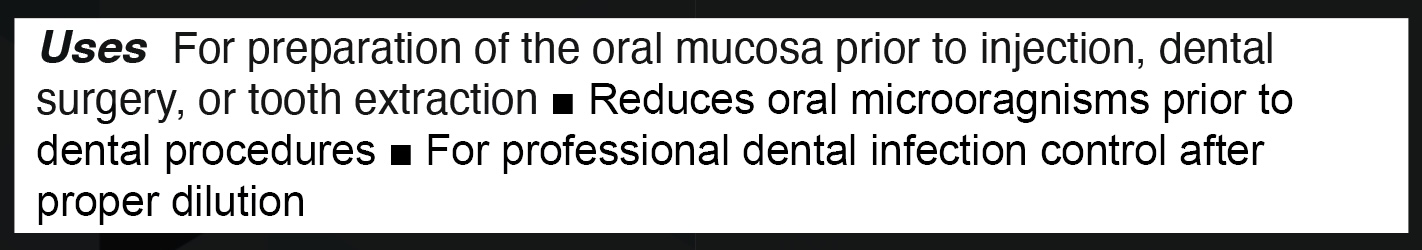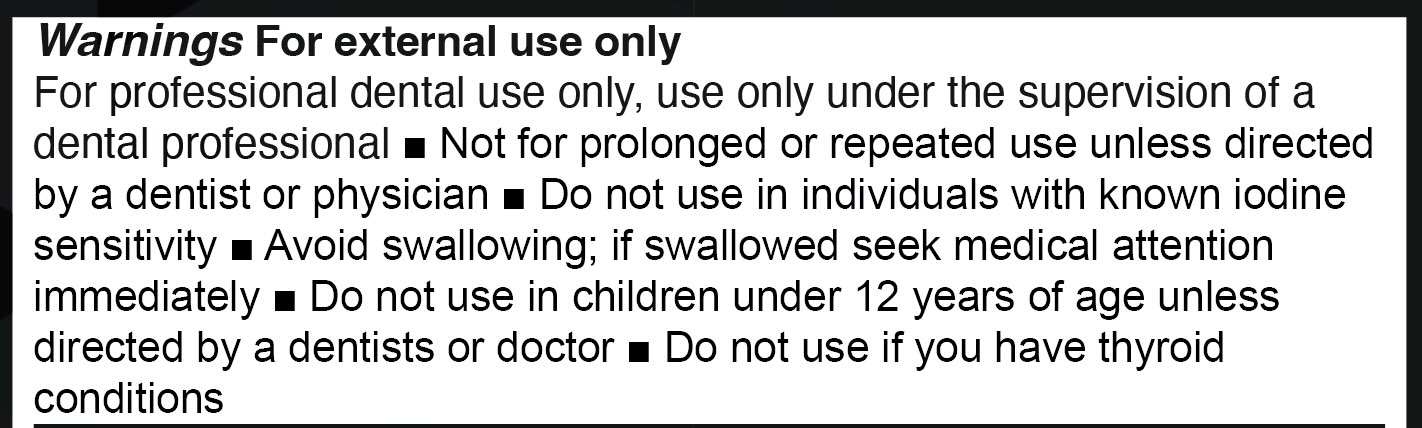 DRUG LABEL: Povi-One
NDC: 57511-0611 | Form: LIQUID
Manufacturer: Elevate Oral Care
Category: otc | Type: HUMAN OTC DRUG LABEL
Date: 20250918

ACTIVE INGREDIENTS: POVIDONE-IODINE 1 mg/10 mL
INACTIVE INGREDIENTS: ANHYDROUS CITRIC ACID; WATER; SODIUM PHOSPHATE, DIBASIC, ANHYDROUS; POLYSORBATE 80; SODIUM CITRATE; GLYCERIN

Povi-One